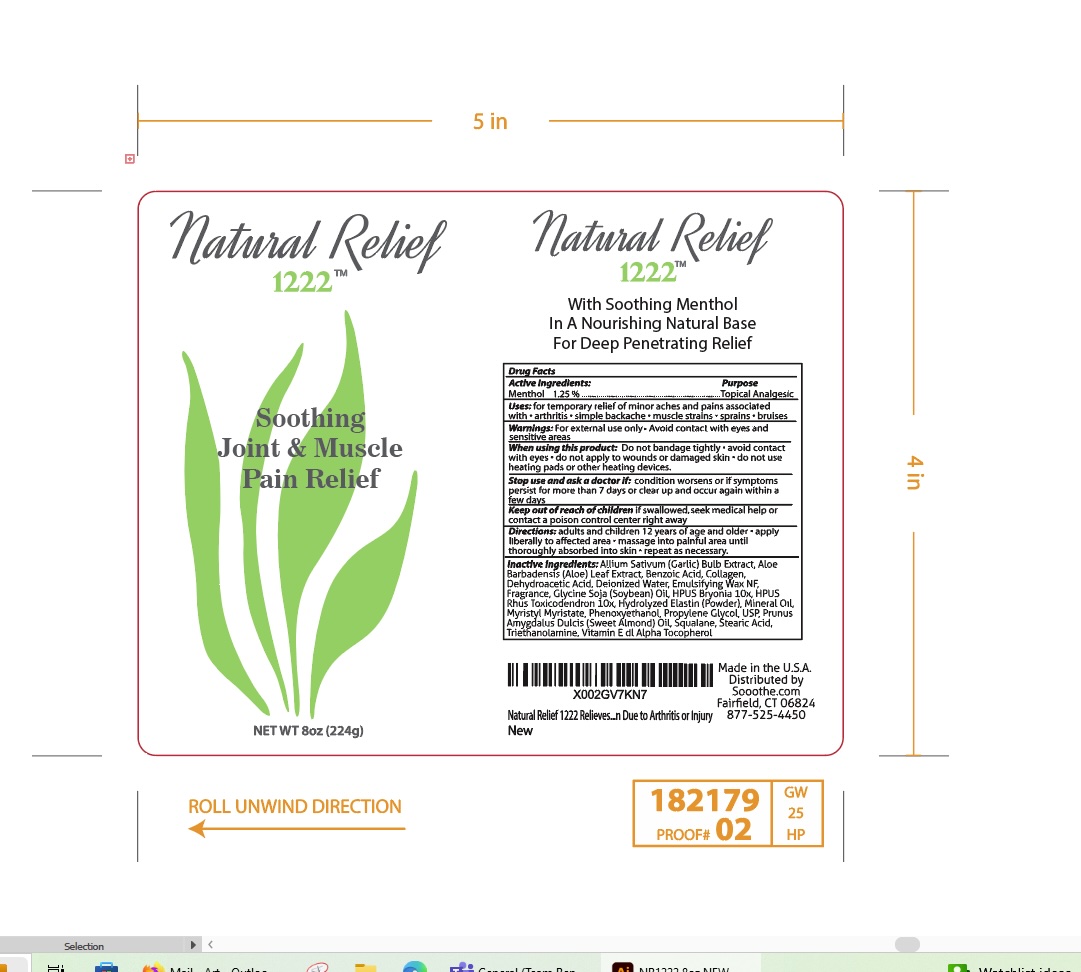 DRUG LABEL: Natural Relief 1222
NDC: 76348-711 | Form: LOTION
Manufacturer: RENU LABORATORIES, INC.
Category: otc | Type: HUMAN OTC DRUG LABEL
Date: 20240115

ACTIVE INGREDIENTS: MENTHOL 2.8 g/224 g
INACTIVE INGREDIENTS: STEARIC ACID; PHENOXYETHANOL; GARLIC; TOXICODENDRON PUBESCENS LEAF; PROPYLENE GLYCOL; MYRISTYL MYRISTATE; BRYONIA ALBA ROOT; SQUALANE; WHITE WAX; WATER; TROLAMINE; .ALPHA.-TOCOPHEROL; HYDROLYZED BOVINE ELASTIN (BASE; 1000 MW); MARINE COLLAGEN, SOLUBLE; ALMOND OIL; SOYBEAN OIL; ALOE VERA LEAF; BENZOIC ACID; DEHYDROACETIC ACID; TETRASODIUM EDETATE DIHYDRATE

Natural Relief 1222 Menthol

ACTIVE INGREDIENT

Menthol. . . . 1.25 percent

WARNINGS

For external use only Avoid contact with eyes and sensitive areas. Stop use and ask a doctor if condition worsens or if symptoms persist for more than 7 days or clear up and occur again within a few days.

Stop use and ask a doctor if condition persists for more than 3 days or worsens.

Keep out of reach of children.

PURPOSE

Topical Analgesic

INDICATIONS AND USAGE

Temporary relief of minor aches and pains associated with

- arthritis
- simple backache
- muscle strains
- sprains
- bruises

Directions

adults and children 12 years of age and older - apply liberally to affected area

- massage into painful area until thoroughly absorbed into skin
- repeat as necessary

OTHER SAFETY INFORMATION

Store at 68 ° to 77° F.

STATEMENT OF IDENTITY

Natural Relief 1222 HOMEOPATHIC JOINT & MUSCLE PAIN RELIEF

INACTIVE INGREDIENT

Allium Sativum (Garlic) Bulb Extract, Aloe Barbadensis (Aloe) Leaf Extract, Benzoic Acid, Collagen, Dehydroacetic Acid, Deionized Water, Emulsifying Wax NF, Fragrance, Glycine Soja (Soybean) Oil, HPUS Bryonia 10x, HPUS Rhus Toxicodendron 10x, Hydolyzed Elastin (Powder), Mineral Oil, Myristyl Myristate, Phenoxyethanol, Propylene Glycol, USP, Prunus Amygdalus Dulcis (Sweet Almond Oil), Squalane, Stearic Acid, Triethanolamine, Vitamin E dl Alpha Tocopherol

RECENT MAJOR CHANGES

Added a better explanation of uses 1.22.2024

Directions modified for a better explanation 1.22.2024

When using this product:

- Do not bandage tightly -
- avoid contact with eyes
- do not apply to wounds or damaged skin
- do not use heating pads or other heating devices

Keep out of reach of children

If swallowed, seek medical help or contact a poison control center right away

STATEMENT OF IDENTITY

Natural Relief 1222

Soothing Joint & Muscle

Pain Relief

Natural Relief 1222 Label

LABEL ART